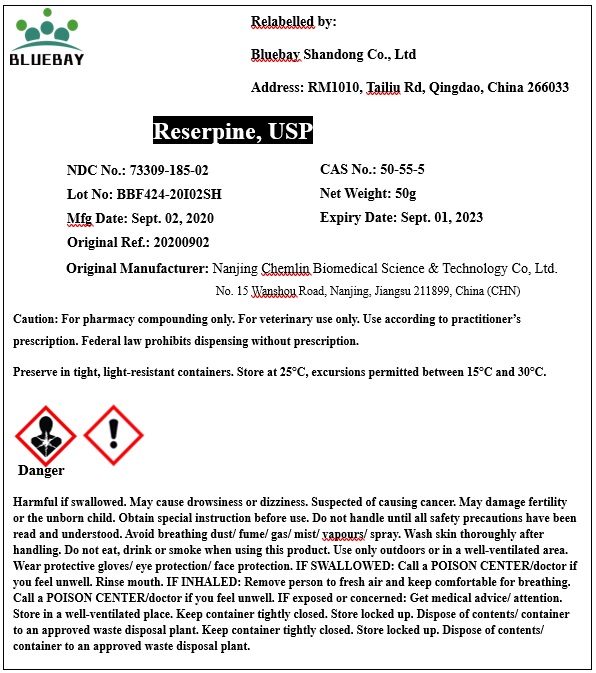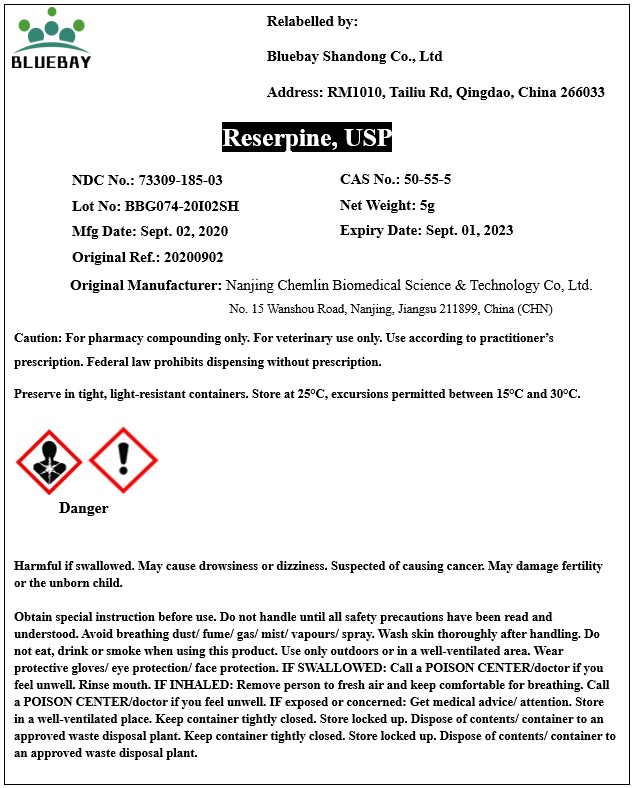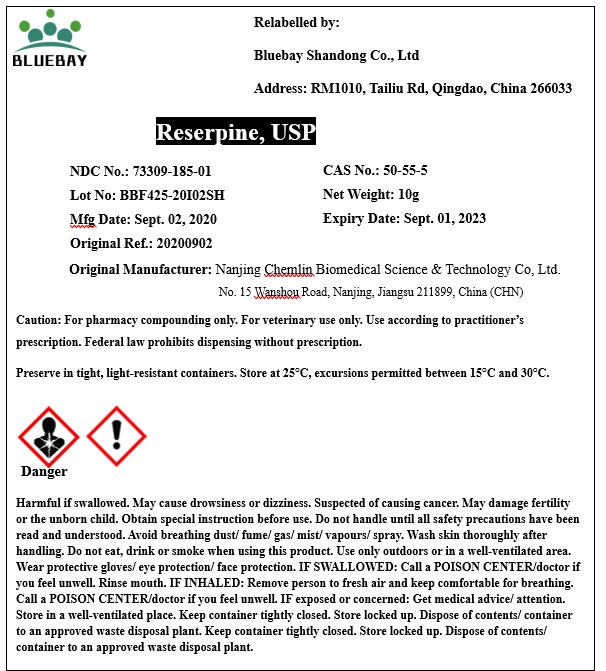 DRUG LABEL: Reserpine
NDC: 73309-185 | Form: POWDER
Manufacturer: BLUEBAY SHANDONG CO.,LTD
Category: other | Type: BULK INGREDIENT
Date: 20210129

ACTIVE INGREDIENTS: RESERPINE 1 g/1 g

Reserpine